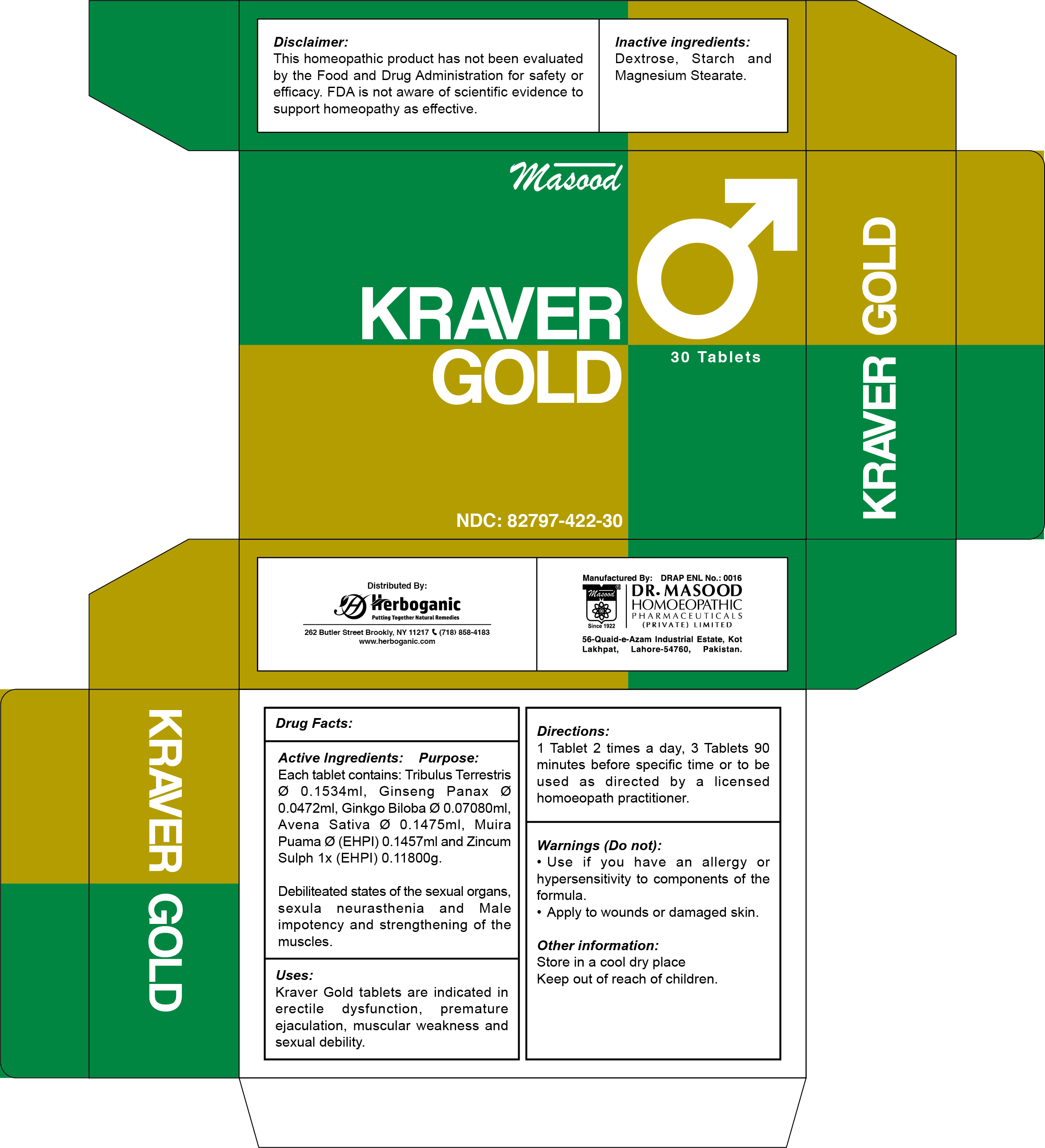 DRUG LABEL: KRAVER GOLD
NDC: 82797-422 | Form: TABLET, COATED
Manufacturer: Dr. Masood Homeopathic Pharmaceuticals Private Limited
Category: homeopathic | Type: HUMAN OTC DRUG LABEL
Date: 20240709

ACTIVE INGREDIENTS: ZINC SULFATE 0.118 mg/600 mg; TRIBULUS TERRESTRIS WHOLE 0.1534 mg/600 mg; AVENA SATIVA WHOLE 0.1475 mg/600 mg; PTYCHOPETALUM OLACOIDES WHOLE 0.1457 mg/600 mg; GINKGO BILOBA WHOLE 0.0708 mg/600 mg; PANAX GINSENG WHOLE 0.0472 mg/600 mg
INACTIVE INGREDIENTS: STARCH, CORN 12 mg/600 mg; DEXTROSE 420 mg/600 mg; MAGNESIUM STEARATE 6 mg/600 mg

Dosage and Administration

1 Tablet 2 times a day, 3 Tablets 90 minutes before a specific time or as directed by a licensed homeopathic practitioner

Indications and Usage

Kraver Gold tablets are indicated in erectile dysfunction, premature ejaculation, muscular weakness, and sexual debility

Inactive Ingredients

Dextrose

Starch

Magnesium stearate

ACTIVE INGREDIENT

TRIBULUS TERRESTRIS

PANAX GINSENG

GINKGO BILOBA

AVENA SATIVA

MUIRA PUAMA (PTYCHOPETALUM)

ZINC SULFATE

Keep out of the reach of children

Keep this and all other medicines out of the reach of children

Purpose

Ingredient Purpose

TRIBULUS TERRESTRIS: Debilitated states of the sexual organs, sexual neurasthenia

GINSENG panax: Male impotency and strengthening of the muscles.

GINKGO BILOBA: Dilated arteries of male sexual organs by improving blood circulation to the body

AVENA SATIVA: Increases the male hormone (testosterone) level in the blood

MUIRA PUAMA: Considered a valuable remedy for impotence

ZINCUM SULPH: Muscles cramps. Hypochondriasis due to masturbation

Warnings

Do not:

- use if you have an allergy or hypersensitivity to components of the formula

Stop use and ask a doctor if:

- condition worsens
- If symptoms persists for more than 7 days

Do not use if blister seal is broken

Keep in a cool and dry place